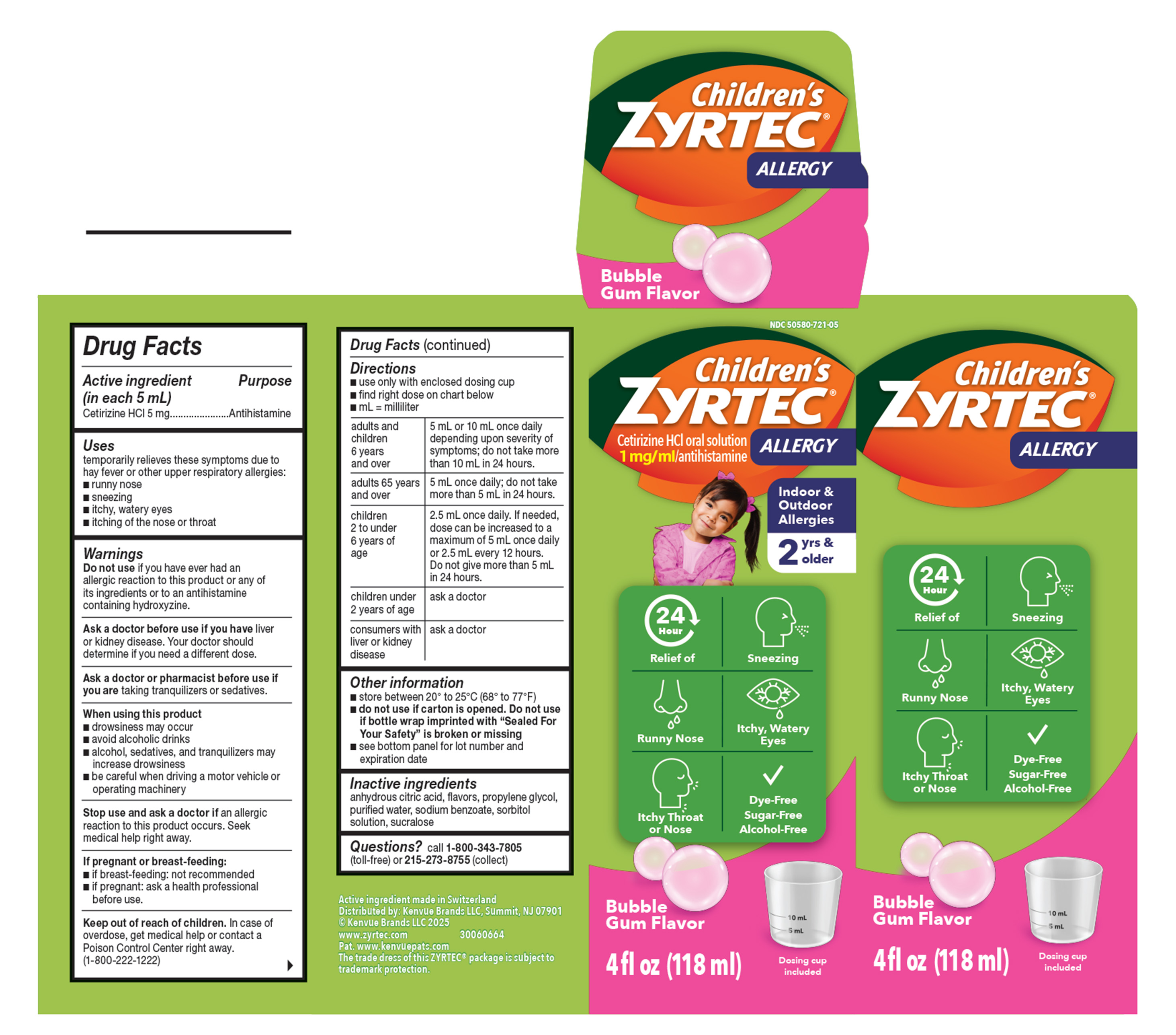 DRUG LABEL: Childrens Zyrtec Allergy
NDC: 50580-721 | Form: SYRUP
Manufacturer: Kenvue Brands LLC
Category: otc | Type: HUMAN OTC DRUG LABEL
Date: 20260119

ACTIVE INGREDIENTS: CETIRIZINE HYDROCHLORIDE 5 mg/5 mL
INACTIVE INGREDIENTS: SORBITOL SOLUTION; ANHYDROUS CITRIC ACID; PROPYLENE GLYCOL; WATER; SODIUM BENZOATE; SUCRALOSE

Children's ZYRTEC®
ALLERGY

Drug Facts

Active ingredient (in each 5 mL)

Cetirizine HCl 5 mg

Purpose

Antihistamine

Uses

temporarily relieves these symptoms due to hay fever or other upper respiratory allergies:

- runny nose
- sneezing
- itchy, watery eyes
- itching of the nose or throat

Warnings

Do not use if you have ever had an allergic reaction to this product or any of its ingredients or to an antihistamine containing hydroxyzine.

Ask a doctor before use if you have liver or kidney disease. Your doctor should determine if you need a different dose.

Ask a doctor or pharmacist before use if you are taking tranquilizers or sedatives.

When using this product

- drowsiness may occur
- avoid alcoholic drinks
- alcohol, sedatives, and tranquilizers may increase drowsiness
- be careful when driving a motor vehicle or operating machinery
- in rare cases, you may experience itching after stopping cetirizine. Consult your healthcare provider if this happens.

Stop use and ask a doctor if an allergic reaction to this product occurs. Seek medical help right away.

If pregnant or breast-feeding:

- if breast-feeding: not recommended
- if pregnant: ask a health professional before use.

Keep out of reach of children. In case of overdose, get medical help or contact a Poison Control Center right away. (1-800-222-1222)

Directions

- use only with enclosed dosing cup
- find right dose on chart below
- mL = milliliter

adults and children 6 years and over | 5 mL or 10 mL once daily depending upon severity of symptoms; do not take more than 10 mL in 24 hours.
adults 65 years and over | 5 mL once daily; do not take more than 5 mL in 24 hours.
children 2 to under 6 years of age | 2.5 mL once daily. If needed, dose can be increased to a maximum of 5 mL once daily or 2.5 mL every 12 hours. Do not give more than 5 mL in 24 hours.
children under 2 years of age | ask a doctor
consumers with liver or kidney disease | ask a doctor

Other information

- store between 20° to 25°C (68° to 77°F)
- do not use if carton is opened. Do not use if bottle wrap imprinted with “Sealed For Your Safety” is broken or missing
- see bottom panel for lot number and expiration date

Inactive ingredients

anhydrous citric acid, flavors, propylene glycol, purified water, sodium benzoate, sorbitol solution, sucralose

Questions?

call 1-800-343-7805 (toll-free) or 215-273-8755 (collect).

PRINCIPAL DISPLAY PANEL

NDC 50580-721-05

Children's
ZYRTEC®
ALLERGY

Cetirizine HCl oral solution
1 mg / ml/antihistamine

Indoor & Outdoor Allergies

2 yrs & older

24 Hour
Relief of

- Sneezing
- Runny Nose
- Itchy, Watery Eyes
- Itchy Throat or Nose

Dye-Free

Sugar-Free

Alcohol-Free

Bubble Gum Flavor

4 fl oz (118 ml)

Dosing Cup Included